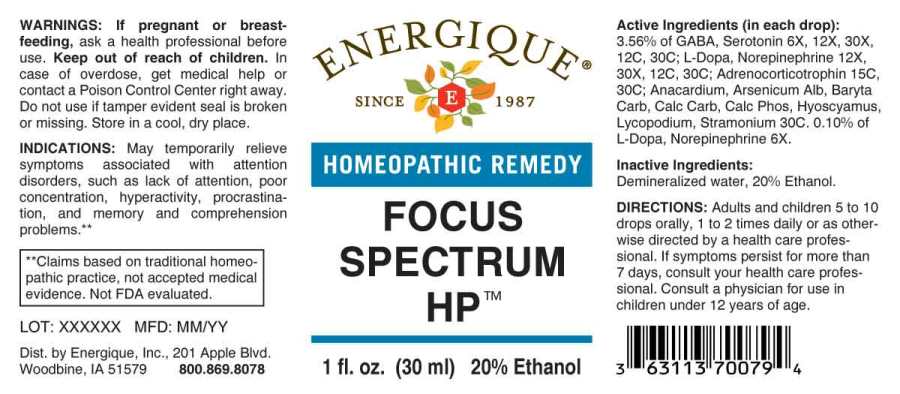 DRUG LABEL: Focus Spectrum HP
NDC: 44911-0584 | Form: LIQUID
Manufacturer: Engergique, Inc.
Category: homeopathic | Type: HUMAN OTC DRUG LABEL
Date: 20241024

ACTIVE INGREDIENTS: .GAMMA.-AMINOBUTYRIC ACID 6 [hp_X]/1 mL; LEVODOPA 6 [hp_X]/1 mL; NOREPINEPHRINE BITARTRATE 6 [hp_X]/1 mL; SEROTONIN HYDROCHLORIDE 6 [hp_X]/1 mL; CORTICOTROPIN 15 [hp_C]/1 mL; SEMECARPUS ANACARDIUM JUICE 30 [hp_C]/1 mL; ARSENIC TRIOXIDE 30 [hp_C]/1 mL; BARIUM CARBONATE 30 [hp_C]/1 mL; OYSTER SHELL CALCIUM CARBONATE, CRUDE 30 [hp_C]/1 mL; TRIBASIC CALCIUM PHOSPHATE 30 [hp_C]/1 mL; HYOSCYAMUS NIGER 30 [hp_C]/1 mL; LYCOPODIUM CLAVATUM SPORE 30 [hp_C]/1 mL; DATURA STRAMONIUM 30 [hp_C]/1 mL
INACTIVE INGREDIENTS: WATER; ALCOHOL

DRUG FACTS:

ACTIVE INGREDIENTS:

(in each drop): 3.56% of GABA (Gamma-Aminobutyric Acid) 6X, 12X, 30X, 12C, 30C, Serotonin (Hydrochloride) 6X, 12X, 30X,12C, 30C; L-Dopa 12X, 30X, 12C, 30C, Norepinephrine (Bitartrate) 12X, 30X, 12C, 30C; Adrenocorticotrophin 15C, 30C; Anacardium Orientale 30C, Arsenicum Album 30C, Baryta Carbonica 30C, Calcarea Carbonica 30C, Calcarea Phosphorica 30C, Hyoscyamus Niger 30C, Lycopodium Clavatum 30C, Stramonium 30C, 0.10% of L-Dopa 6X, Norepinephrine (Bitartrate) 6X.

INDICATIONS:

May temporarily relieve symptoms associated with attention disorders, such as lack of attention, poor concentration, hyperactivity, procrastination, and memory and comprehension problems.**

**Claims based on traditional homeopathic practice, not accepted medical evidence. Not FDA evaluated.

WARNINGS:

If pregnant or breast-feeding, ask a health professional before use.

Keep out of reach of children. In case of overdose, get medical help or contact a Poison Control Center right away.

Do not use if tamper evident seal is broken or missing.

Store in cool, dry place.

Keep out of reach of children. In case of overdose, get medical help or contact a Poison Control Center right away.

DIRECTIONS:

Adults and children 5 to 10 drops orally, 1 to 2 times daily or as otherwise directed by a health care professional. If symptoms persist for more than 7 days, consult your health care professional. Consult a physician for use in children under 12 years of age.

INDICATIONS:

May temporarily relieve symptoms associated with attention disorders, such as lack of attention, poor concentration, hyperactivity, procrastination, and memory and comprehension problems.**

**Claims based on traditional homeopathic practice, not accepted medical evidence. Not FDA evaluated.

INACTIVE INGREDIENTS:

Demineralized water, 20% Ethanol.

QUESTIONS:

Dist. by Energique, Inc.

201 Apple Blvd.

Woodbine, IA 51579 800.869.8078

PACKAGE LABEL DISPLAY:

ENERGIQUE

SINCE 1987

HOMEOPATHIC REMEDY

FOCUS SPECTRUM HP

1 fl. oz. (30 ml)